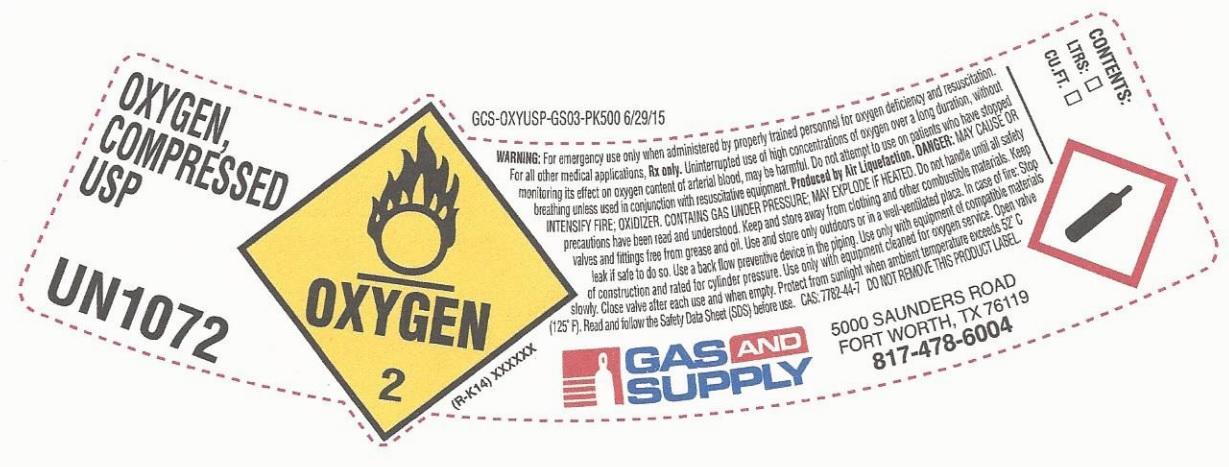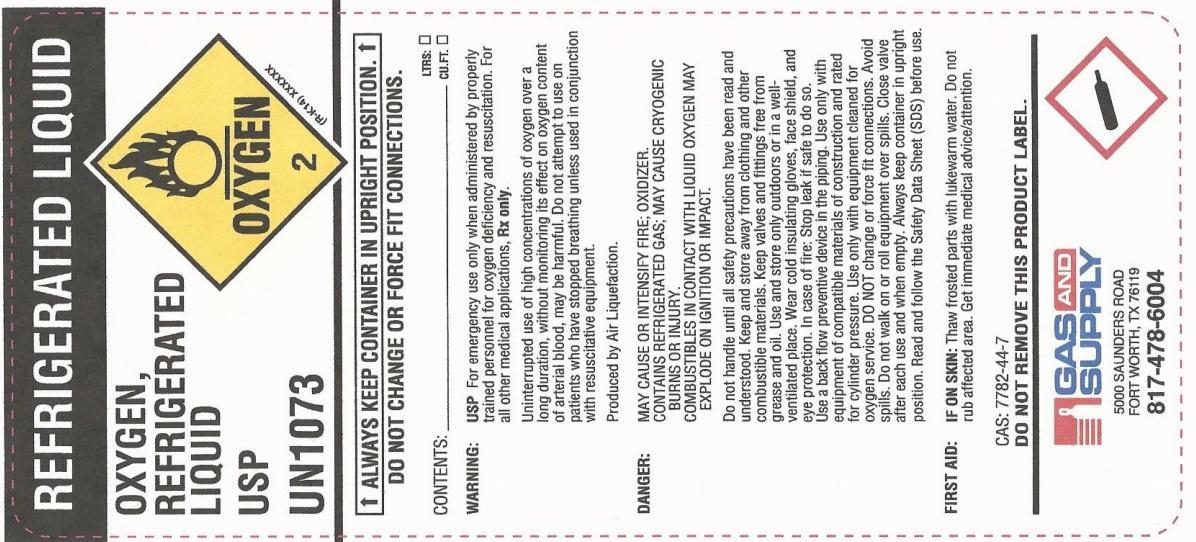 DRUG LABEL: Oxygen
NDC: 70101-001 | Form: GAS
Manufacturer: Gas and Supply
Category: prescription | Type: HUMAN PRESCRIPTION DRUG LABEL
Date: 20251203

ACTIVE INGREDIENTS: OXYGEN 995 mL/1 L

Oxygen

PACKAGE LABEL

OXYGEN, COMPRESSED USP
US1072
OXYGEN 2
WARNING: For emergency use only when administered by properly trained personnel for oxygen deficiency and resuscitation. For all other medical applications, Rx only. Uninterrupted use of high concentrations of oxygen over a long duration, without monitoring its effect on oxygen content of arterial blood, may be harmful. Do not attempt to use on patients who have stopped breathing unless used in conjunction with resuscitative equipment. Produced by Air Liquefaction. DANGER: MAY CAUSE OR INTENSIFY FIRE; OXIDIZER. CONTAINS GAS UNDER PRESSURE; MAY EXPLODE IF HEATED. Do not handle until all safety precautions have been read and understood. Keep and store away from clothing and other combustible materials. Keep valves and fittings free from grease and oil. Use and store only outdoors or in a well-ventilated place. In case of fire: Stop leak if safe to do so. Use a back flow preventive device in the piping. Use only with equipment of compatible materials of construction and rated for cylinder pressure. Use only with equipment cleaned for oxygen service. Open valve slowly. Close valve after each use and when empty. Protect from sunlight when ambient temperature exceeds 52 degrees C (125 degrees F). Read and follow the Safety Data Sheet (SDS) before use. CAS: 7782-44-7. DO NOT REMOVE THIS PRODUCT LABEL
CONTENTS: LTRS: CU.FT.
GAS AND SUPPLY
5000 SAUNDERS ROAD
FORT WORTH, TX 76119
817-478-6004

PACKAGE LABEL

REFRIGERATED LIQUID
OXYGEN, REFRIGERATED LIQUID USP
UN1073
OXYGEN 2
ALWAYS KEEP CONTAINER IN UPRIGHT POSITION.
DO NOT CHANGE OR FORCE FIT CONNECTIONS.
CONTENTS: LTRS… CU.FT.
WARNING: USP For emergency use only when administered by properly trained personnel for oxygen deficiency and resuscitation. For all other medical applications, Rx only.
Uninterrupted use of high concentrations of oxygen over a long duration, without monitoring its effect on oxygen content of arterial blood, may be harmful. Do not attempt to use on patients who have stopped breathing unless used in conjunction with resuscitative equipment.
Produced by Air Liquefaction.
DANGER: MAY CAUSE OR INTENSITY FIRE; OXIDIZER. CONTAINS REFRIGERATED GAS; MAY CAUSE CRYOGENIC BURNS OR INJURY. COMBUSTIBLES IN CONTACT WITH LIQUID OXYGEN MAY EXPLODE ON IGNITION OR IMPACT.
Do not handle until all safety precautions have been read and understood. Keep and store away from clothing and other combustible materials. Keep valves and fittings free from grease and oil. Use and store only outdoors or in a well-ventilated place. Wear cold insulating gloves, face shield, and eye protection. In case of fire: Stop leak if safe to do so. Use a back flow preventive device in the piping. Use only with equipment of compatible materials of construction and rated for cylinder pressure. Use only with equipment cleaned for oxygen service. DO NOT change or force fit connections. Avoid spills. Do not walk on or roll equipment over spills. Close valve after each use and when empty. Always keep container in upright position. Read and follow the Safety Data Sheet (SDS) before use.
FIRST AID: IF ON SKIN: Thaw frosted parts with lukewarm water. Do not rub affected area. Get immediate medical advice/attention.
CAS: 7782-44-7
DO NOT REMOVE THIS PRODUCT LABEL.
GAS AND SUPPLY
5000 SAUNDERS ROAD
FORT WORTH, TX 76119
817-478-6004